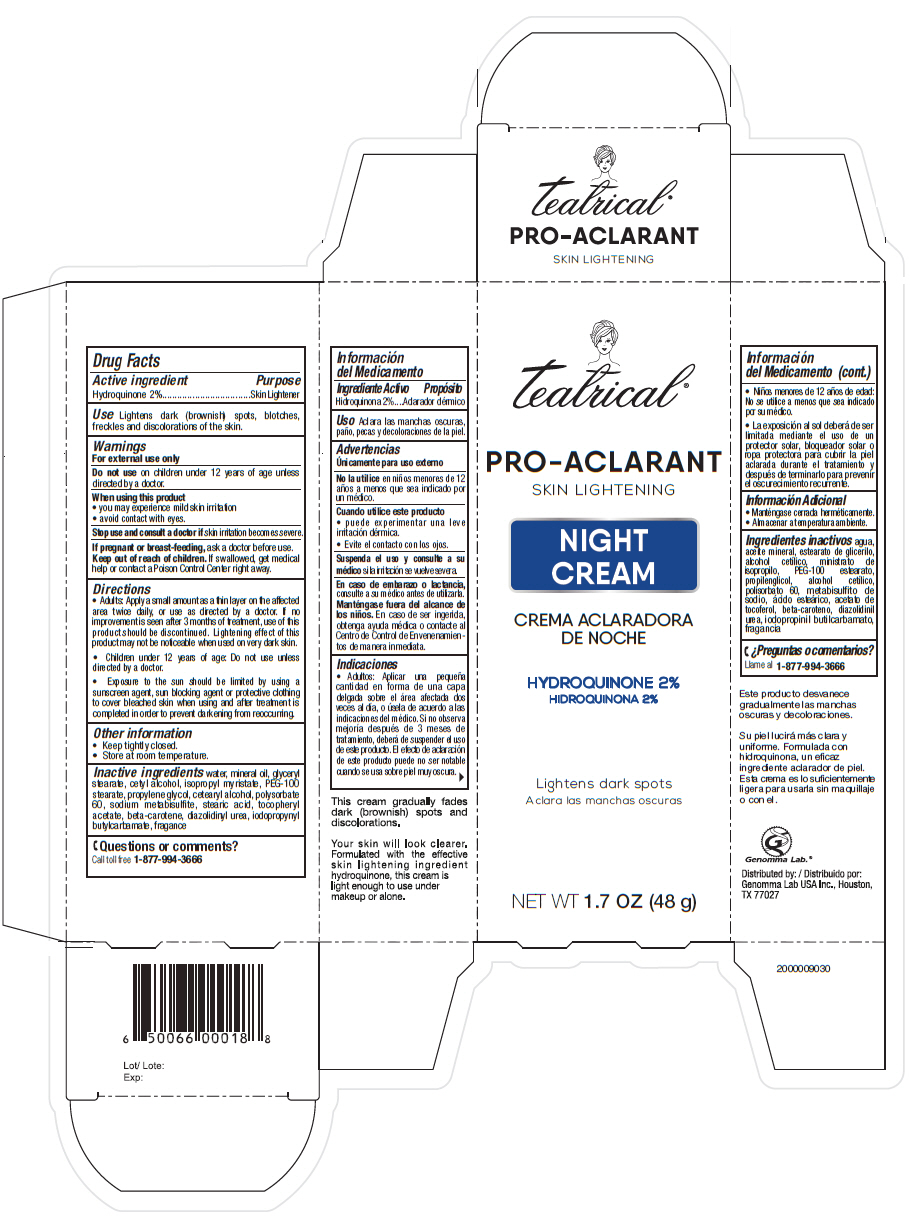 DRUG LABEL: Teatrical Pro-Aclarant Skin Lightening
NDC: 50066-072 | Form: CREAM
Manufacturer: Genomma Lab USA
Category: otc | Type: HUMAN OTC DRUG LABEL
Date: 20200422

ACTIVE INGREDIENTS: Hydroquinone 20 mg/1 g
INACTIVE INGREDIENTS: Mineral oil; Isopropyl myristate; Propylene Glycol; Cetyl alcohol; Polysorbate 60; PEG-100 stearate

Teatrical® Pro-Aclarant Skin Lightening Cream

Drug Facts

Active ingredient

Hydroquinone 2%

Purpose

Skin Lightener

Use

Lightens dark (brownish) spots, blotches, freckles and discolorations of the skin.

Warnings

For external use only

Do not use on children under 12 years of age unless directed by a doctor.

When using this product

- you may experience mild skin irritation
- avoid contact with eyes.

Stop use and consult a doctor if skin irritation becomes severe.

PREGNANCY OR BREAST FEEDING

If pregnant or breast-feeding, ask a doctor before use.

Keep out of reach of children. If swallowed, get medical help or contact a Poison Control Center right away.

Directions

- Adults: Apply a small amount as a thin layer on the affected area twice daily, or use as directed by a doctor. If no improvement is seen after 3 months of treatment, use of this product should be discontinued. Lightening effect of this product may not be noticeable when used on very dark skin.
- Children under 12 years of age: Do not use unless directed by a doctor.
- Exposure to the sun should be limited by using a sunscreen agent, sun blocking agent or protective clothing to cover bleached skin when using and after treatment is completed in order to prevent darkening from reoccurring.

Other information

- Keep tightly closed.
- Store at room temperature.

Inactive ingredients

water, mineral oil, glyceryl stearate, cetyl alcohol, isopropyl myristate, PEG-100 stearate, propylene glycol, cetearyl alcohol, polysorbate 60, sodium metabisulfite, stearic acid, tocopheryl acetate, beta-carotene, diazolidinyl urea, iodopropynyl butylcarbamate, fragance

Questions or comments?

Call toll free 1-877-994-3666

Distributed by:
Genomma Lab USA Inc., Houston,
TX 77027

PRINCIPAL DISPLAY PANEL - 48 g Tube Carton

teatrical®

PRO-ACLARANT
SKIN LIGHTENING

NIGHT
CREAM

HYDROQUINONE 2%

Lightens dark spots

NET WT 1.7 OZ (48 g)